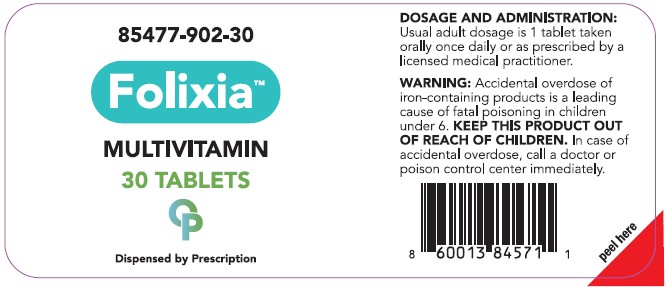 DRUG LABEL: Folixia
NDC: 85477-902 | Form: TABLET
Manufacturer: Oncora Pharma, LLC
Category: prescription | Type: HUMAN PRESCRIPTION DRUG LABEL
Date: 20260212

ACTIVE INGREDIENTS: FERROUS BISGLYCINATE 20 mg/1 1; POTASSIUM IODIDE 0.15 mg/1 1; PYRIDOXINE HYDROCHLORIDE 26 mg/1 1; BETA CAROTENE 0.3 mg/1 1; ASCORBIC ACID 60 mg/1 1; CHOLECALCIFEROL 0.1 mg/1 1; BIOTIN 0.28 mg/1 1; FOLIC ACID 1.67 mg/1 1; CYANOCOBALAMIN 0.013 mg/1 1; CALCIUM CARBONATE 80 mg/1 1; MAGNESIUM OXIDE 25 mg/1 1; .ALPHA.-TOCOPHEROL ACETATE, DL- 4.5 mg/1 1
INACTIVE INGREDIENTS: STEARIC ACID; CELLULOSE, MICROCRYSTALLINE; SILICON DIOXIDE; MAGNESIUM STEARATE; MALTODEXTRIN; CROSCARMELLOSE SODIUM

Folixia

DESCRIPTION

Folixia is a prescription multivitamin/multimineral dietary supplement.

INDICATIONS AND USAGE

Folixia is a prescription multivitamin/multi-mineral dietary supplement formulated for the clinical dietary management of a subuoptimal nutritional status in patients where advanced folate, vitamin B supplementation, and maintenance of good health is needed.

CONTRAINDICATIONS

Folixia is contraindicated in patients with a known hypersensitivity to any of the ingredients.

PRECAUTIONS

Folic acid alone is improper therapy in the treatment of pernicious anemia and other megaloblastic anemias where Vitamin B 12 deficient. Folic acid in doses above 1.0 mg daily may obscure pernicious anemia in that hematologic remission can occur while neurological manifestations progress.

WARNINGS

WARNING Accidental overdose of iron-containing products is a leading cause of fatal poising in children under 6. Keep this product out of the reach of children. In the case of accidental overdose, call a doctor or poison control center immediately.

ADVERSE REACTIONS

Allergic sensitization has been reported following both oral and parenteral administration of folic acid. You should call your doctor for medical advice about serious adverse events. To reports adverse side effects or to obtain product information, contact Oncora Pharma at 888-321-2821.

DOSAGE AND ADMINISTRATION

One tablet daily or as directed by a physician.

HOW SUPPLIED

Bottles of 30 Tablets (85477-902-30). Tablet is light blue, oblong.

*Oncora Pharma does not represent this products code to be National Drug Code
(NDC). Products codes are formatted according to standard industry practice, to meet the
formatting requirement by pedigree reporting and supply-chain control including
pharmacies.
This products is a prescription-folate with or without other dietary ingredients the - due to
increased folate levels increased risk associated with masking B12 deficiency (pernicious
anemia) requires administration under the care of a licensed medical practitioner(64 FR
8760). 1-3 the most appropriate way to ensure pedigree reporting consistent with these
regulatory guidelines and safety monitoring is to dispense this product only by prescription.
This is not an Orange Book product. This product may be administered only under a
physician's supervision and all prescriptions using this product shall be pursuant to state
statues as applicable. The ingredients, indication or claims of this product are not to be
construed to be Drug claims.
1.) Federal register Notice of August 2, 1973 (39 FR 20750)
2.) Federal Register Notice of October 17, 1980 (45 FR 69043, 69044)
3.) Federal register notice of March 5, 1996 (61 FR 8760)
Storage and Handing

STORAGE AND HANDLING

STORAGE: Store at 20- 25 degree C (68-77 F) excersions permitted to 15-30 degree C (59-86 F) {See USP controlled Room Temperature} Avoid excessive heat, light and moisture.

TAMPER EVIDENT: Do not use if seal is broken or missing.

MADE IN USA
Distributed by:
888-321-2821
Oncora Pharma
Dallas, TX 75161

OTHER SAFETY INFORMATION

KEEP THIS AND ALL MEDICATIONS OUT OF THE REACH OF CHILDREN